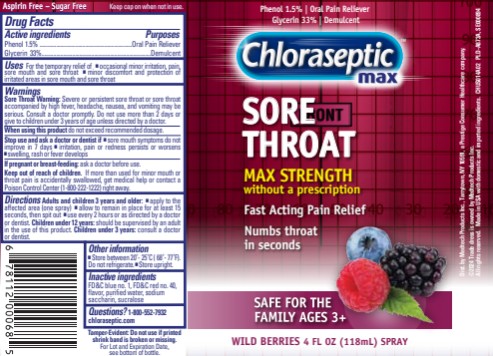 DRUG LABEL: Chloraseptic Sore Throat Max
NDC: 67172-937 | Form: SPRAY
Manufacturer: Prestige Brands Holdings, Inc.
Category: otc | Type: HUMAN OTC DRUG LABEL
Date: 20251023

ACTIVE INGREDIENTS: PHENOL 15 mg/1 mL; GLYCERIN 330 mg/1 mL
INACTIVE INGREDIENTS: FD&C BLUE NO. 1; FD&C RED NO. 40; WATER; SACCHARIN SODIUM; SUCRALOSE

Chloraseptic Sore Throat Spray Max

Drug Facts

Active Ingredients

Phenol 1.5%

Purpose

Oral Pain Reliever

Active Ingredients

Glycerin 33%

Purpose

Demulcent

Uses

for the temporary relief of ■ occasional minor irritation, pain, sore mouth and sore throat ■ minor discomfort and protection of irritated areas in sore mouth and sore throat

Warnings

Sore Throat Warning: Severe or persistent sore throat or sore throat accompanied by high fever, headache, nausea, and vomiting may be serious. Consult a doctor promptly. Do not use more than 2 days or give to children under 3 years of age unless directed by a doctor.

When using this product

do not exceed recommended dosage.

If pregnant or breast-feeding,

ask a doctor before use.

Keep out of reach of children.

If more than used for minor mouth or throat pain is accidentally swallowed, get medical help or contact a Poison Control Center (1-800-222-1222) right away.

Directions

Adults and children 3 years of age and older:

- apply to the affected area (one spray)
- allow to remain in place for at least 15 seconds, then spit out
- use every 2 hours or as directed by a doctor or dentist

Children under 12 years of age should be supervised by an adult in the use of this product.

Children under 3 years of age: consult a doctor or dentist.

Other Information

- store between 20-25C (68-77F). Do not refrigerate
- Store upright

Inactive ingredients

FD&C blue no. 1, FD&C red no. 40, flavor, purified water, sodium saccharin, sucralose

Questions?

1-800-552-7932 Chloraseptic.com

PRINCIPAL DISPLAY PANEL

Chloraseptic® Max Sore Throat

Phenol Oral Anesthetic /Demulcent Spray 4 fl oz (118 mL) | Wild Berries